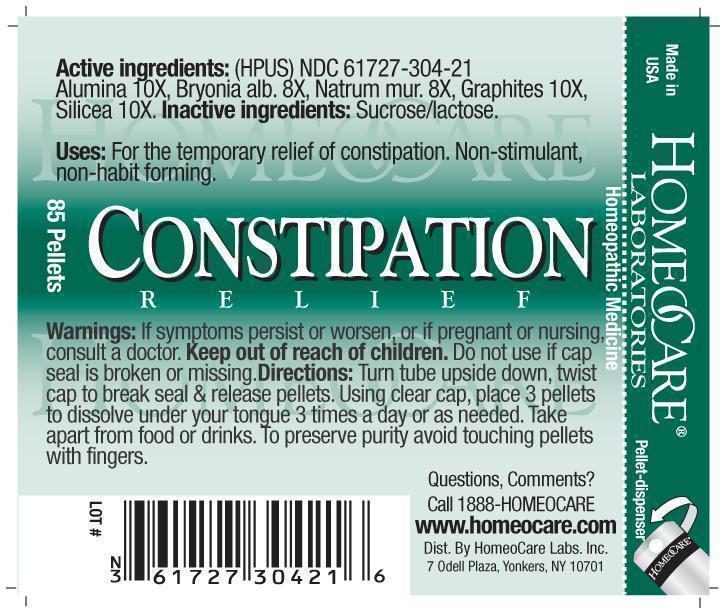 DRUG LABEL: Constipation Relief
NDC: 61727-304 | Form: PELLET
Manufacturer: Homeocare Laboratories
Category: homeopathic | Type: HUMAN OTC DRUG LABEL
Date: 20260112

ACTIVE INGREDIENTS: ALUMINUM OXIDE 10 [hp_X]/4 g; BRYONIA ALBA ROOT 8 [hp_X]/4 g; SODIUM CHLORIDE 8 [hp_X]/4 g; GRAPHITE 10 [hp_X]/4 g; SILICON DIOXIDE 10 [hp_X]/4 g
INACTIVE INGREDIENTS: SUCROSE; LACTOSE

Constipation Relief

Active Ingredients:

Alumina 10X, Bryonia alb. 8X, Natrum mur. 8X, Graphites 10X, Silicea 10X.

Purpose:

For the temporary relief of constipation. Non-stimulant, non-habit forming.

Keep out of reach of children.

Indications & Usage:

Turn tube upside down, twist cap to break seal & release pellets. Using clear cap, place 3 pellets to dissolve under your tongue 3 times a day or as needed. Take apart from food or drinks. To preserve purity avoid touching pellets with fingers.

Warnings:

If symptoms persist or worsen, or if pregnant or nursing, consult a doctor.

Dosage & Administration:

Turn tube upside down, twist cap to break seal & release pellets. Using clear cap, place 3 pellets to dissolve under your tongue 3 times a day or as needed. Take apart from food or drinks. To preserve purity avoid touching pellets with fingers.

Inactive Ingredients:

Sucrose/lactose.

Constipation Relief

Homeopathic Medicine

85 Pellets

hcl_label_constipation-2012.jpg